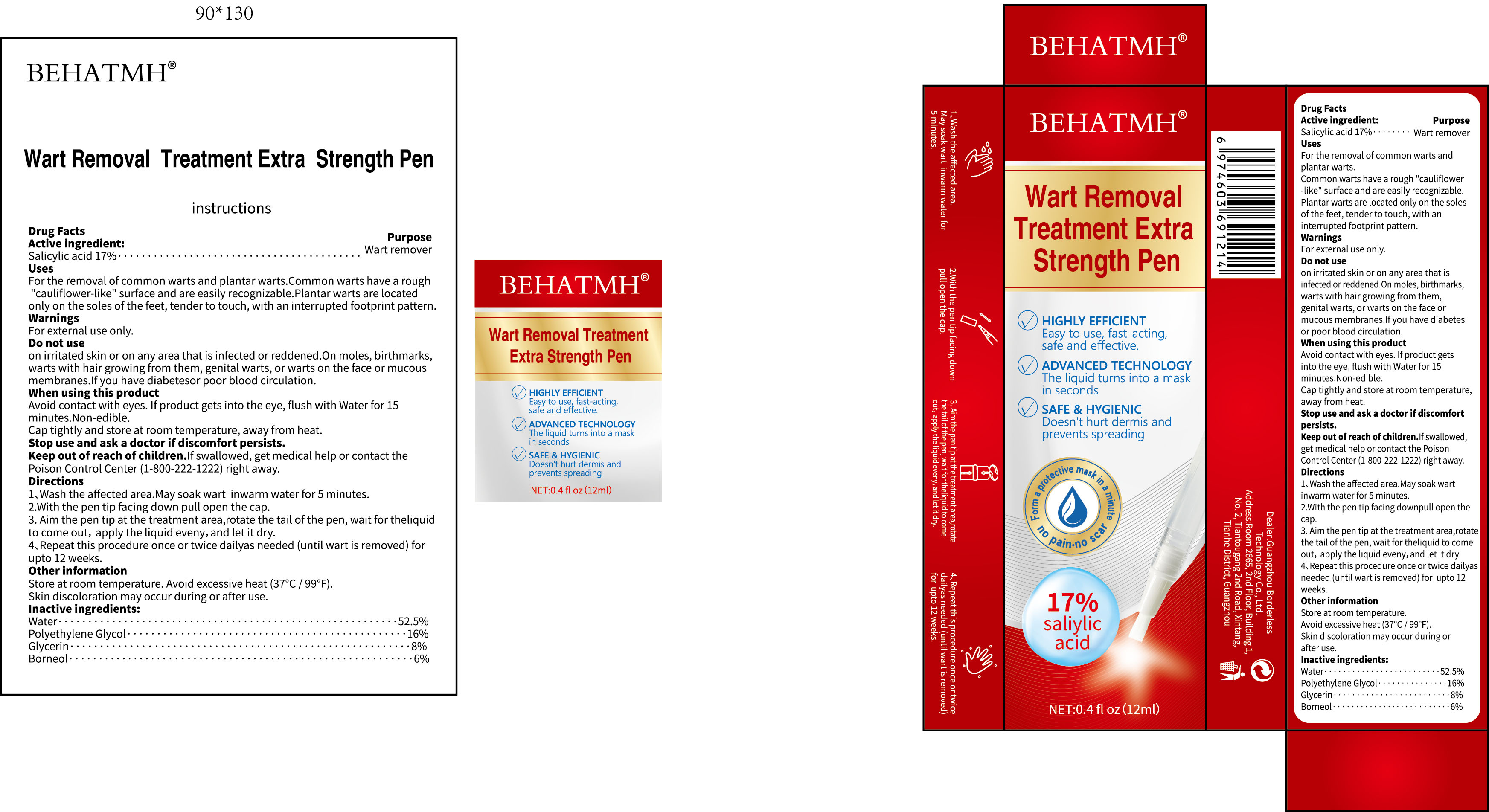 DRUG LABEL: BEHATMH 17% Salicylic acid Wart Remover Serum Pen
NDC: 85304-015 | Form: LIQUID
Manufacturer: Guangzhou Borderless Technology Co., Ltd.
Category: otc | Type: HUMAN OTC DRUG LABEL
Date: 20250924

ACTIVE INGREDIENTS: SALICYLIC ACID 17 g/100 mL
INACTIVE INGREDIENTS: WATER; GLYCERIN; BORNEOL; POLYETHYLENE GLYCOL, UNSPECIFIED

85304-015 BEHATMH 17% Salicylic acid Wart Remover Serum Pen

ACTIVE INGREDIENT

Salicylic acid 17%

PURPOSE

Wart remover

INDICATIONS AND USAGE

For the removal of common warts and plantar warts.Common warts have a rough'cauliflower-like" surface and are easily recognizable.Plantar warts are locatedonly on the soles of the feet, tender to touch, with an interrupted footprint pattern.

WARNINGS

For external use only.

DO NOT USE

on irritated skin or on any area that is infected or reddened.On moles, birthmarkswarts with hair growing from them, genital warts, or warts on the face or mucousmembranes.lfyou have diabetesor poor blood circulation.

WHEN USING

Avoid contact with eyes. lf product gets into the eye, flush with Water for 15minutes.Non-edible.
Cap tightly and store at room temperature, away from heat.

Keep out of reach of children.lfswallowed, get medical help or contact thePoison ControlCenter(1-800-222-1222)right away.

Stop use and ask a doctor if discomfort persists.

DOSAGE AND ADMINISTRATION

1、Wash the affected area.May soak wart inwarm water for 5 minutes.
2.With the pen tip facing down pull open the cap.
3. Aim the pen tip at the treatment area,rotate the tail of the pen, wait for theliquidto come out, apply the liquid eveny, and let it dry.
4、 Repeat this procedure once or twice dailyas needed (until wart is removed) forupto 12 weeks.

INACTIVE INGREDIENT

Water
Polyethylene Glycol
Glycerin
Borneol